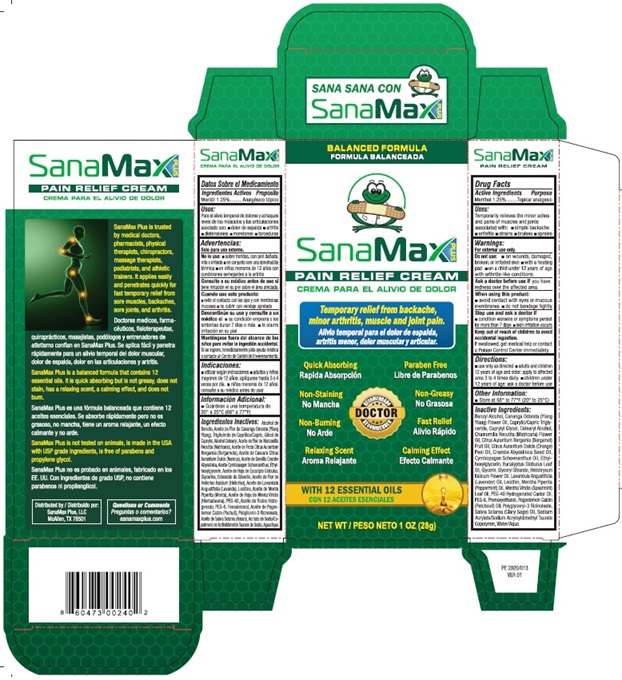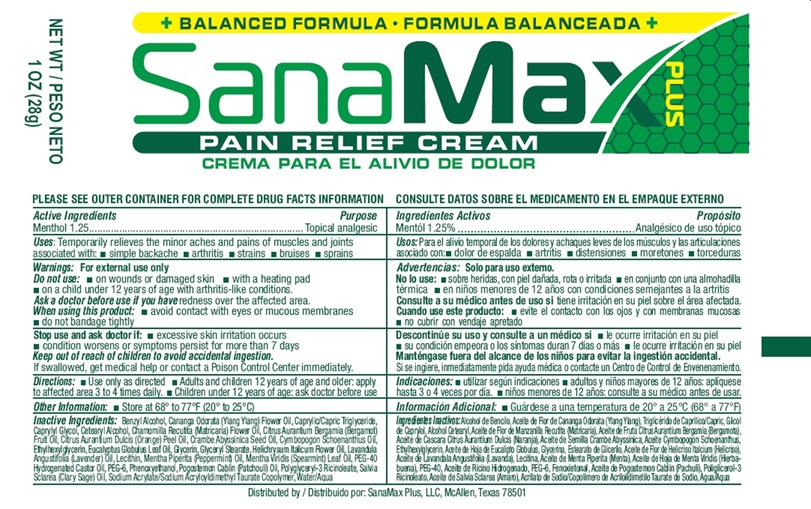 DRUG LABEL: Pain Relief Cream
NDC: 72425-201 | Form: CREAM
Manufacturer: SanaMax Plus LLC
Category: otc | Type: HUMAN OTC DRUG LABEL
Date: 20241230

ACTIVE INGREDIENTS: MENTHOL 1.25 g/100 g
INACTIVE INGREDIENTS: BENZYL ALCOHOL; CANANGA ODORATA FLOWER; MEDIUM-CHAIN TRIGLYCERIDES; CAPRYLYL GLYCOL; CETOSTEARYL ALCOHOL; CHAMOMILE FLOWER OIL; BERGAMOT OIL; ORANGE OIL; CRAMBE HISPANICA SUBSP. ABYSSINICA SEED OIL; CYMBOPOGON SCHOENANTHUS OIL; ETHYLHEXYLGLYCERIN; EUCALYPTUS OIL; GLYCERIN; GLYCERYL MONOSTEARATE; HELICHRYSUM ITALICUM FLOWER OIL; LAVENDER OIL; LECITHIN, SUNFLOWER; PEPPERMINT OIL; SPEARMINT OIL; POLYOXYL 40 HYDROGENATED CASTOR OIL; POLYETHYLENE GLYCOL 300; PHENOXYETHANOL; POGOSTEMON CABLIN LEAF OIL; POLYGLYCERYL-3 RICINOLEATE; CLARY SAGE OIL; SODIUM ACRYLATE/SODIUM ACRYLOYLDIMETHYLTAURATE COPOLYMER (4000000 MW); WATER

SanaMax PLUS PAIN RELIEF CREAM

Drug Facts

Active Ingredients Menthol 1.25%

Purpose Topical analgesic

INDICATIONS AND USAGE

Uses: temporarily relieves the minor aches and pains of muscles and
joints associated with: ■ simple backache ■ arthritis ■ strains ■ bruises ■ sprains

Warnings
For external use only.

Do not use: ■ on wounds, damaged, broken, or irritated skin

■ with a heating pad ■ on a child under 12 years of age with

arthritis-like conditions.

Ask a doctor before use if you have redness over the affected area.

When using this product ■ avoid contact with eyes or mucous membrane

■ do not bandage tightly

Stop use and ask a doctor if
■ condition worsens or symptoms persist for more than 7 days
■ skin irritation occurs

Keep out of reach of children to avoid accidental ingestion.

If swallowed, get medical help or contact a Poison Control Center immediately.

Directions
■ use only as directed ■ adults and children 12 years of age and
older: apply to affected area 3 to 4 times daily
■ children under 12 years of age: ask a doctor before use

Other information:

■ Store at 68° to 77°F (20° to 25°C)

Inactive Ingredients:
Benzyl Alcohol, Cananga Odorata (Ylang
Ylang) Flower Oil, Caprylic/Capric Trigl-
yceride, Caprylyl Glycol, Cetearyl Alcohol,
Chamomilla Recutita (Matricaria) Flower
Oil, Citrus Aurantium Bergamia (Bergamot)
Fruit Oil, Citrus Aurantium Dulcis (Orange)
Peel Oil, Crambe Abyssinica Seed Oil,
Cymbopogon Schoenanthus Oil, Ethyl-
hexylglycerin, Eucalyptus Globulus Leaf
Oil, Glycerin, Glyceryl Stearate, Helichrysum
Italicum Flower Oil, Lavandula Angustifolia
(Lavender) Oil, Lecithin, Mentha Piperita
(Peppermint) Oil, Mentha Viridis (Spearmint)
Leaf Oil, PEG-40 Hydrogenated Castor Oil,
PEG-6, Phenoxyethanol, Pogostemon Cablin
(Patchouli) Oil, Polyglyceryl-3 Ricinoleate,
Salvia Sclarea (Clary Sage) Oil, Sodium
Acrylate/Sodium Acryloyldimethyl Taurate
Copolymer, Water/Aqua

Principal Display Package Labeling

SanaMax PLUS

BALANCED FORMULA

SanaMax PLUS

PAIN RELIEF CREAM

Temporary relief from backache,

minor arthritis, muscle and joint pain.

Quick Absorbing Paraben Free

Non Staining Non-Greasy

Non-Burning Fast Relief

Relaxing Scent Calming Effect

DOCTOR RECOMMENDED

WITH 12 ESSENTIAL OILS

NET WT 1 OZ (28g)

SanaMax PLUS

PAIN RELIEF CREAM

SanaMax Plus is trusted
by medical doctors,
pharmacists, physical
therapists, chiropractors,
massage therapists,
podiatrists, and athletic
trainers. It applies easily
and penetrates quickly for
fast temporary relief from
sore muscles, backaches,
sore joints, and arthritis.

SanaMax Plus is a balanced formula that contains 12
essential oils. It is quick absorbing but is not greasy, does not
stain, has a relaxing scent, a calming effect, and does not
burn.

SanaMax Plus is not tested on animals, is made in the USA
with USP grade ingredients, is free of parabens, and
propylene glycol.

Distributed by: Questions or Comments
SanaMax Plus LLC sanamaxplus.com
McAllen, TX 78501

NDC 72425-201-02

8 60473 00240 2

PE 2020/013

VER 01

BOX

TUBE

res